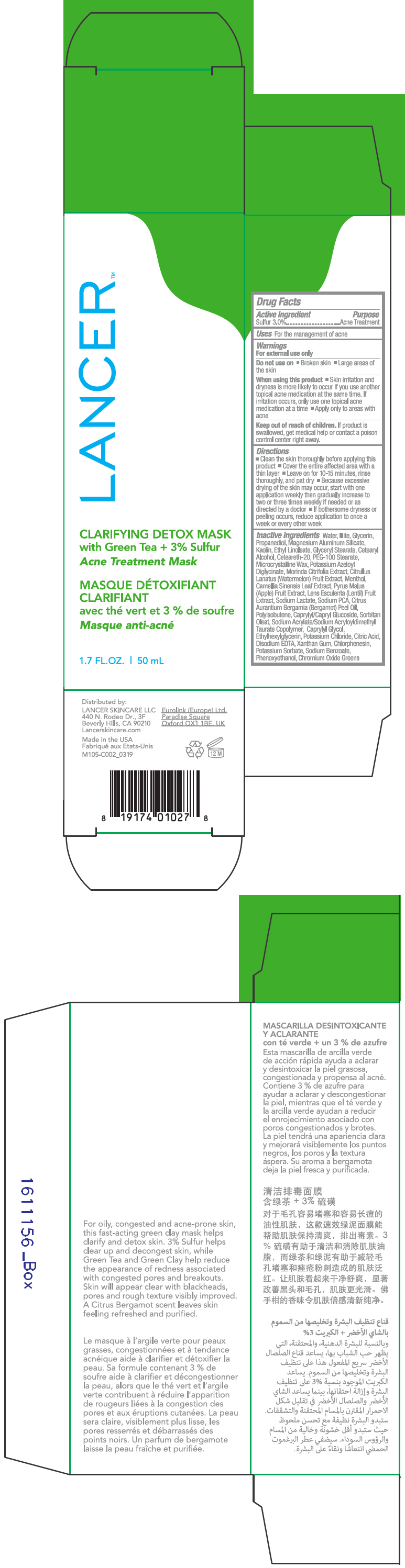 DRUG LABEL: Clarifying Detox Mask with Green Tea plus Sulfur 
NDC: 72704-105 | Form: CREAM
Manufacturer: Lancer Skincare LLC.
Category: otc | Type: HUMAN OTC DRUG LABEL
Date: 20230119

ACTIVE INGREDIENTS: Sulfur 3 g/100 mL
INACTIVE INGREDIENTS: Water; Ledikite; Glycerin; Propanediol; Magnesium Aluminum Silicate; Kaolin; Ethyl Linoleate; Glyceryl Monostearate; Cetostearyl Alcohol; Polyoxyl 20 Cetostearyl Ether; PEG-100 Stearate; Microcrystalline Wax; Potassium Azeloyl Diglycinate; Morinda Citrifolia Leaf; Watermelon; Menthol, Unspecified Form; Green Tea Leaf; Apple; Lens Culinaris Fruit; Sodium Lactate; Sodium Pyrrolidone Carboxylate; Bergamot Oil; Caprylyl/Capryl Oligoglucoside; SORBITAN MONOOLEATE; SODIUM ACRYLATE/SODIUM ACRYLOYLDIMETHYLTAURATE COPOLYMER (4000000 MW); Caprylyl Glycol; Ethylhexylglycerin; Potassium Chloride; Citric Acid Monohydrate; Edetate Disodium Anhydrous; Xanthan Gum; Chlorphenesin; Potassium Sorbate; Sodium Benzoate; Phenoxyethanol; Chromic Oxide

Clarifying Detox Mask with Green Tea plus Sulfur
Acne Treatment Mask

Drug Facts

Active Ingredient

Sulfur 3.0%

Purpose

Acne Treatment

Uses

For the management of acne

Warnings

For external use only

Do not use on

- Broken skin
- Large areas of the skin

When using this product

- Skin irritation and dryness is more likely to occur if you use another topical acne medication at the same time. If irritation occurs, only use one topical acne medication at a time
- Apply only to areas with acne

Keep out of reach of children. If product is swallowed, get medical help or contact a poison control center right away.

Directions

- Clean the skin thoroughly before applying this product
- Cover the entire affected area with a thin layer
- Leave on for 10-15 minutes, rinse thoroughly, and pat dry
- Because excessive drying of the skin may occur, start with one application weekly then gradually increase to two or three times weekly if needed or as directed by a doctor
- If bothersome dryness or peeling occurs, reduce application to once a week or every other week

Inactive Ingredients

Water, Illite, Glycerin, Propanediol, Magnesium Aluminum Silicate, Kaolin, Ethyl Linoleate, Glyceryl Stearate, Cetearyl Alcohol, Ceteareth-20, PEG-100 Stearate, Microcrystalline Wax, Potassium Azeloyl Diglycinate, Morinda Citrifolia Extract, Citrullus Lanatus (Watermelon) Fruit Extract, Menthol, Camellia Sinensis Leaf Extract, Pyrus Malus (Apple) Fruit Extract, Lens Esculenta (Lentil) Fruit Extract, Sodium Lactate, Sodium PCA, Citrus Aurantium Bergamia (Bergamot) Peel Oil, Polyisobutene, Caprylyl/Capryl Glucoside, Sorbitan Oleat, Sodium Acrylate/Sodium Acryloyldimethyl Taurate Copolymer, Caprylyl Glycol, Ethylhexylglycerin, Potassium Chloride, Citric Acid, Disodium EDTA, Xanthan Gum, Chlorphenesin, Potassium Sorbate, Sodium Benzoate, Phenoxyethanol, Chromium Oxide Green

Distributed by:
LANCER SKINCARE LLC
440 N. Rodeo Dr., 3F
Beverly Hills, CA 90210

PRINCIPAL DISPLAY PANEL - 50 mL Tube Carton

LANCER™

CLARIFYING DETOX MASK
with Green Tea + 3% Sulfur

Acne Treatment Mask

1.7 FL.OZ. | 50 mL